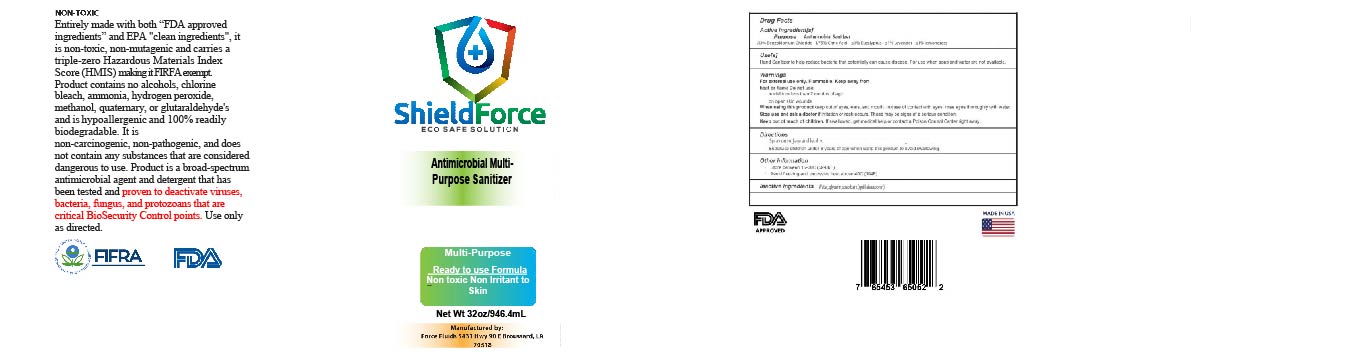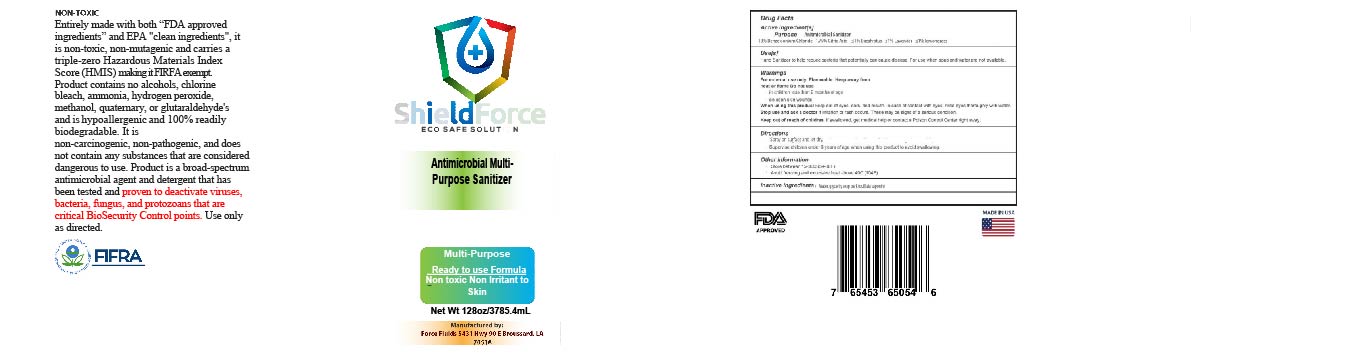 DRUG LABEL: ShieldForce ESS
NDC: 80743-151 | Form: LIQUID
Manufacturer: Force Fluids LLC
Category: otc | Type: HUMAN OTC DRUG LABEL
Date: 20201118

ACTIVE INGREDIENTS: LAVANDULA ANGUSTIFOLIA FLOWER 0.0002 g/100 mL; BENZALKONIUM 0.13 g/100 mL; CYMBOPOGON CITRATUS LEAF 0.0002 g/100 mL; EUCALYPTUS OIL 0.0002 g/100 mL
INACTIVE INGREDIENTS: QUILLAJA SAPONARIA BARK; GLYCERIN; WATER

This is a sanitizer manufactured according to the Temporary Policy for Preparation of Certain Alcohol-Based Hand Sanitizer Products During the Public Health Emergency (CoViD-19); Guidance for Industry.

The hand sanitizer is manufactured using only the following United States Pharmacopoeia (USP) grade ingredients in the preparation of the product (percentage in final product formulation) consistent with World Health Organization (WHO) recommendations:

1. .13% Benzalklonium Chloride
2. 1.75% citric acid
3. <1% lemongrass
4. <1% eucalyptus
5. <1% lavender

The firm does not add other active or inactive ingredients. Different or additional ingredients may impact the quality and potency of the product.

Active Ingredient(s)

Benzalklonium Chloride, citric acid

PURPOSE

Antiseptic, Antimiicrobial

Use

Sanitizer to help reduce bacteria that potentially can cause disease.

Warnings

For external use only. Non flammable.

Do not use

- in children less than 2 months of age
- on open skin wounds

When using this product keep out of eyes, ears, and mouth. In case of contact with eyes, rinse eyes thoroughly with water.
Stop use and ask a doctor if irritation or rash occurs. These may be signs of a serious condition.
Keep out of reach of children. If swallowed, get medical help or contact a Poison Control Center right away.

Stop use and ask a doctor if irritation or rash occurs. These may be signs of a serious condition.

Keep out of reach of children. If swallowed, get medical help or contact a Poison Control Center right away.

Directions

- Place enough product on hands to cover all surfaces. Let dry.

Other information

- Store between 15-30C (59-86F)
- Avoid freezing and excessive heat above 40C (104F)

Inactive ingredients

glycerin, soap bark extract, purified water USP

Package Label - Principal Display Panel

NDC Code: 80743-151-32

NDC Code: 80743-151-17